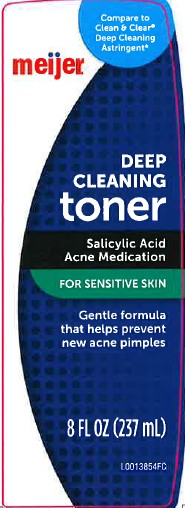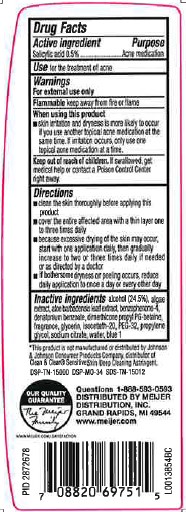 DRUG LABEL: Deep Cleaning Astringent
NDC: 41250-775 | Form: LIQUID
Manufacturer: Meijer, Inc.
Category: otc | Type: HUMAN OTC DRUG LABEL
Date: 20260219

ACTIVE INGREDIENTS: SALICYLIC ACID 5 mg/1 mL
INACTIVE INGREDIENTS: ALCOHOL; ALOE; ALOE VERA LEAF; SULISOBENZONE; DENATONIUM BENZOATE; DIMETHICONE; GLYCERIN; ISOCETETH-20; POLYETHYLENE GLYCOL 1500; PROPYLENE GLYCOL; SODIUM CITRATE; WATER; FD&C BLUE NO. 1

Meijer 875.002/875AD-AE
Astringent

Active Ingredient

Salicylic acid 0.5%

Purpose

Acne medication

Use

For the treatment of acne

Warnings

For external use only

Flammable. Keep away from fire or flame.

When using this product

Skin irritation and dryness is more likely to occur if you use another topical acne medication at the same time. If irritation occurs, only use one topical acne medication at a time.

Keep out of reach of children.

If swallowed, get medical help or contact a Poison Control Center right away.

Directions

- clean the skin thoroughly before applying this product
- cover the entire affected area with a thin layer and rinse thoroughly one to three times daily
- because excessive drying of the skin may occur, start with one application daily, the gradually increase to two or three times daily if needed or as directed by a doctor
- if bothersome dryness or peeling occurs, reduce application to once a day or every other day

Inactive ingredients

alcohol (24.5%), algae extract, aloe barbadensis leaf extract, benzophenone-4, denatonium benzoate, dimethicone propyl PG-betaine, fragrance, glycerin, isoceteth-20, PEG-32, proplene glycol, sodium citrate, water, blue 1

Disclaimer

*This product is not manufactured or distributed by Johnson & Johnson Consumer Products Company, distributor of Clean & ClearSensitive Skin Deep Cleaning Astringent.

ADVERSE REACTION

OUR QUALITY GUARANTEE

The Meijer Family

www.meijer.com/satisfaction

Questions 1-888-593-0593

DISTRIBUTED BY MEIJER DISTRIBUTION INC.

GRAND RAPIDS, MI 49544

www.meijer.com

DSP-TN-15000 DSP-MO-34 SDS-TN-15012

principal display panel

Meijer®

Compare to CLEAN & CLEAR®Deep Cleaning Astringent*

Deep Cleaning Toner

Salicylic acid acne medication

for sensitive skin

Gentle formula that helps prevent new acne pimples

8 FL OZ (237 mL)